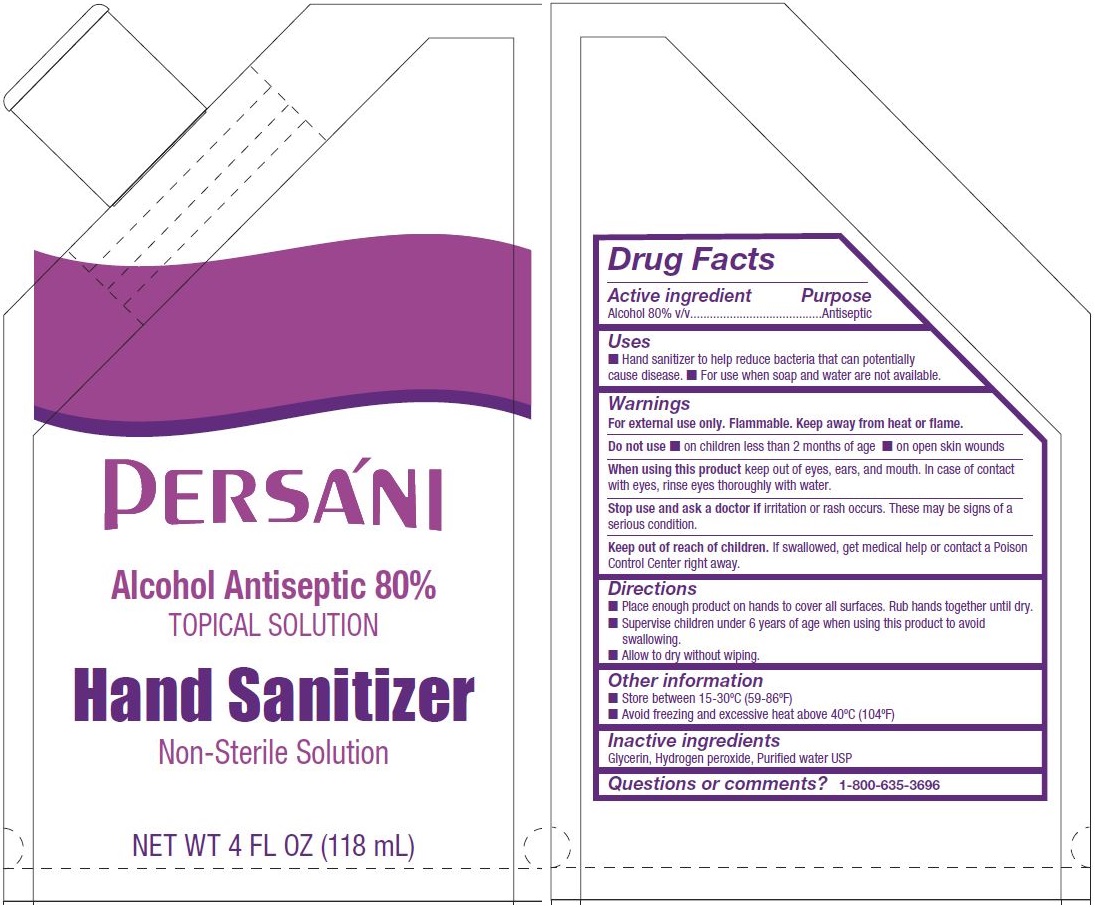 DRUG LABEL: Persani Hand Sanitizer
NDC: 68093-7122 | Form: LIQUID
Manufacturer: Wisconsin Pharmacal Company
Category: otc | Type: HUMAN OTC DRUG LABEL
Date: 20220113

ACTIVE INGREDIENTS: ALCOHOL 80 mL/100 mL
INACTIVE INGREDIENTS: GLYCERIN; HYDROGEN PEROXIDE; WATER

Persani Hand Sanitizer

Drug Facts

Active Ingredient(s)

Active ingredient | Purpose
Alcohol 80% v/v | Antiseptic

Purpose

Antiseptic, Hand Sanitizer

Uses

■ Hand sanitizer to help reduce bacteria that can potentially cause disease.

■ For use when soap and water are not available.

Warnings

For external use only. Flammable. Keep away from heat or flame.

Do not use

■ on children less than 2 months of age ■ on open skin wounds

When using this product keep out of eyes, ears, and mouth. In case of contact
with eyes, rinse eyes thoroughly with water.

Stop use and ask a doctor if irritation or rash occurs. These may be signs of a serious condition.

Keep out of reach of children. If swallowed, get medical help or contact a Poison
Control Center right away.

Directions

■ Place enough product on hands to cover all surfaces. Rub hands together until dry.
■ Supervise children under 6 years of age when using this product to avoid swallowing.
■ Allow to dry without wiping.

Other information

■ Store between 15-30ºC (59-86ºF)
■ Avoid freezing and excessive heat above 40ºC (104ºF)

Inactive ingredients

Glycerin, Hydrogen peroxide, Purified water USP

Questions or comments?

1-800-635-3696

Package Label - Principal Display Panel

PERSÀNI

Alcohol Antiseptic 80%

TOPICAL SOLUTION

Hand Sanitizer

Non-Sterile Solution

NET WT 4 FL OZ (118 mL)